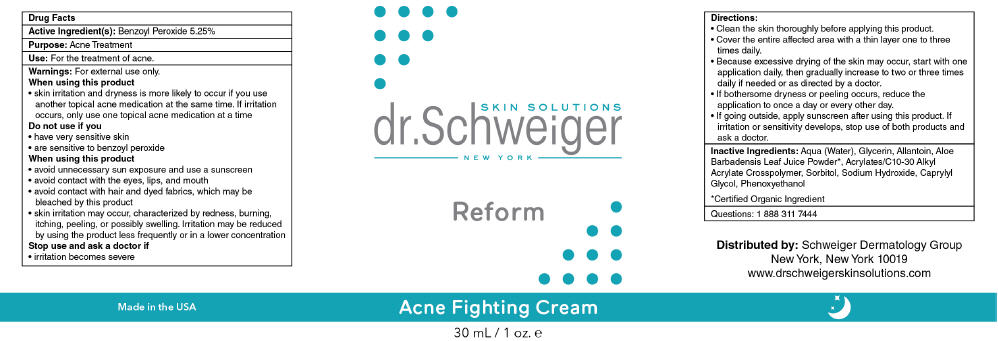 DRUG LABEL: REFORM
NDC: 70911-112 | Form: CREAM
Manufacturer: SCHWEIGER DERMATOLOGY GROUP
Category: otc | Type: HUMAN OTC DRUG LABEL
Date: 20161026

ACTIVE INGREDIENTS: BENZOYL PEROXIDE 52.5 mg/1 mL
INACTIVE INGREDIENTS: WATER; GLYCERIN; ALLANTOIN; ALOE VERA LEAF; ALKYL (C12-15) BENZOATE; SORBITOL; SODIUM HYDROXIDE; CAPRYLIC/CAPRIC ACID; PHENOXYETHANOL

REFORM

Drug Facts

Active Ingredient(s)

Benzoyl Peroxide 5.25%

Purpose

Acne Treatment

Use

For the treatment of Acne.

Warnings

For external use only.

When using this product

- skin irritation and dryness is more likely to occur if you use another topical acne medication at the same time. If irritation occurs, only use one topical acne medication at a time

Do not use if you

- have very sensitive skin
- are sensitive to benzoyl peroxide

When using this product

- avoid unnecessary sun exposure and use a sunscreen
- avoid contact with the eyes, lips, and mouth
- avoid contact with hair and dyed fabrics, which may be bleached by this product
- skin irritation may occur, characterized by redness, burning, itching, peeling, or possibly swelling. Irritation maybe reduced by using the product less frequently or in a lower concentration

Stop use and ask a doctor if

- irritation becomes severe

Directions

- Clean the skin thoroughly before applying this product.
- Cover the entire affected area with a thin layer one to three times daily.
- Because excessive drying of the skin may occur, start with one application daily, then gradually increase to two or three times daily if needed or as directed by a doctor.
- If bothersome dryness or peeling occurs, reduce the application to once a day or every other day.
- If going outside, apply sunscreen after using this product. If irritation or sensitivity develops, stop use of both products and ask a doctor.

Inactive Ingredients

Aqua (Water), Glycerin, Allantoin, Aloe Barbadensis Leaf Juice Powder [Certified Organic Ingredient] , Acrylates/C10-30 Alkyl Acrylate Crosspolymer, Sorbitol, Sodium Hydroxide, Caprylyl Glycol, Phenoxyethanol

Questions

1 888 311 7444

Keep out of Reach of Children.

Distributed by: Schweiger Dermatology Group
New York, New York 10019

PRINCIPAL DISPLAY PANEL - 30 mL Bottle Label

SKIN SOLUTIONS
dr. Schweiger
NEW YORK

Reform

Acne Fighting Cream

30 mL / 1 oz. e